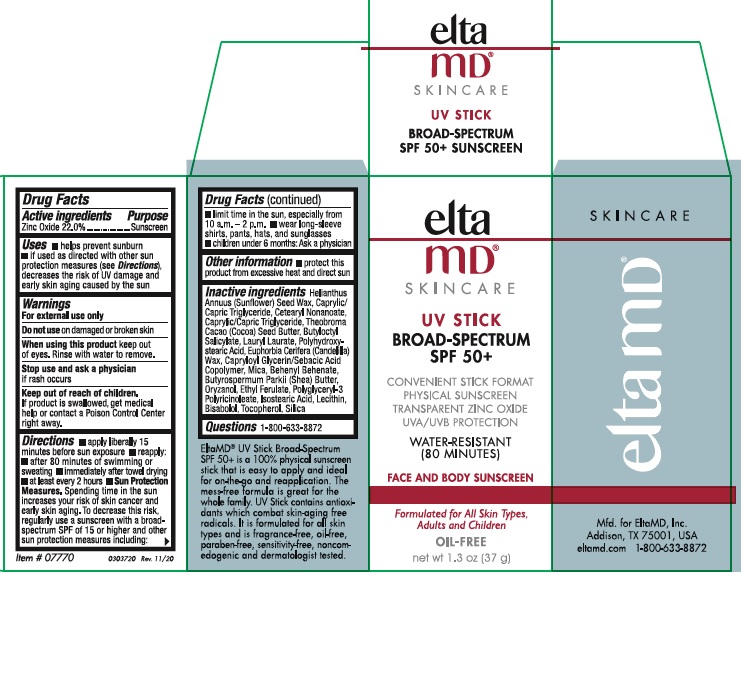 DRUG LABEL: Elta MD Skincare UV Stick Broad Spectrum
NDC: 72043-0495 | Form: STICK
Manufacturer: CP Skin Health Group, Inc
Category: otc | Type: HUMAN OTC DRUG LABEL
Date: 20241204

ACTIVE INGREDIENTS: ZINC OXIDE 22 g/100 g
INACTIVE INGREDIENTS: MEDIUM-CHAIN TRIGLYCERIDES; HELIANTHUS ANNUUS SEED WAX; CETEARYL NONANOATE; COCOA BUTTER; BUTYLOCTYL SALICYLATE; LAURYL LAURATE; POLYHYDROXYSTEARIC ACID (2300 MW); CANDELILLA WAX; CAPRYLOYL GLYCERIN/SEBACIC ACID COPOLYMER (2000 MPA.S); MICA; BEHENYL BEHENATE; SHEA BUTTER; ORYZANOL; ETHYL FERULATE; ISOSTEARIC ACID; LECITHIN, SOYBEAN; POLYGLYCERYL-3 PENTARICINOLEATE; LEVOMENOL; TOCOPHEROL; SILICON DIOXIDE

EltaMD Skincare UV Stick Broad-Spectrum SPF 50+

Active ingredients

Zinc Oxide 22.0%

Purpose

Sunscreen

Uses

- helps prevent sunburn
- if used as directed with other sun protection measures (see Directions), decreases the risk of UV damage and early skin aging caused by the sun

Warnings

For external use only

Do not use

on damaged or broken skin

When using this product

keep out of eyes. Rinse with water to remove.

Stop use and ask a physician

if rash occurs

Keep out of reach of children.

If product is swallowed, get medical help or contact a Poison Control Center right away.

Directions

apply liberally 15 minutes before sun exposure
reapply: after 80 minutes of swimming or sweating: immediately after towel drying: at lear every 2 hours
Sun Protection Measures

Spending time in the sun can increase your riske of skin cancer and early skin aging.
To decrease this risk regularly use a sunscreen with a broad spectrum SPF 15 of 15 or higher and other sun protection measures including:

limit time in the sun, especially from 10 a.m. - 2 p.m.
wear long-sleeve shirts, pants, hats, and sunglasses
children under 6 months:Ask a physician

Other Information

- Protect this product from excessive heat and direct sun

Inactive ingredients

Caprylic/Capric Triglyceride, Helianthys Annuus (Sunflower) Seed Wax, Cerearyl Nonanoate, Theobroma Cacao Cocoa) Seed Butter, Butyloctyl Salicylate, Lauryl Laurate, Polyhydroxystearic Acid, Euphorbia Cerifera (Candelilla) Was, Capryloyl Glycerin/Sebacic Acid Copolymer, Mica, Behenyl Behenate, Butyrospermum Parkii (Shea) Butter, Oryzanol, Ethyl Ferulate, Isostearic Acid, Lecithin, Polyglyceryl-3 Plyricinoleate, Bisabolol, Tocopherol, Silica

PACKAGE LABEL

elta MD® Skincare

UV STICK

BROAD-SPECTRUM SPF 50+

net wt 1.3oz (37 g)